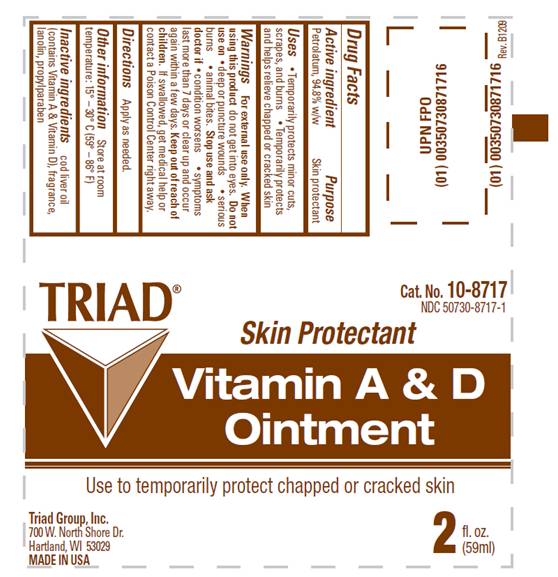 DRUG LABEL: Vitamin A and D
NDC: 50730-8717 | Form: OINTMENT
Manufacturer: H and P Industries, Inc. dba Triad Group
Category: otc | Type: HUMAN OTC DRUG LABEL
Date: 20091229

ACTIVE INGREDIENTS: Petrolatum 0.948 mL/1 mL
INACTIVE INGREDIENTS: cod liver oil; lanolin; propylparaben

DRUG FACTS

ACTIVE INGREDIENT

Petrolatum, 94.8% w/w

PURPOSE

skin protectant

USES

- temporarily protects minor cuts, scrapes and burns
- temporarily protects and helps relieve chapped or cracked skin

WARNINGS

For external use only.

Do not use on

- deep or puncture wounds
- serious burns
- animal bites

When using this product

do not get into eyes

Stop use and ask a doctor if

- condition worsens
- symptoms last more than 7 days or clear up and occur again within a few days

Keep out of reach of children

If swallowed, get medical help or contact a Poison Control Center right away.

DIRECTIONS

Apply as needed.

OTHER INFORMATION

Store at room temperature: 15°- 30° C (59° - 86° F)

INACTIVE INGREDIENTS

cod liver oil (contains Vitamin A and Vitamin D), fragrance, lanolin, propylparaben

PACKAGE INFORMATION

TRIAD
Cat. No. 10-8717
NDC 50730-8717-1
Skin Protectant
VITAMIN A AND D
OINTMENT
Use to temporarily protect chapped or cracked skin
Contents:
2 fl. oz. (59ml)
Triad Group, Inc.
700 West North Shore Drive
Hartland, WI 53029
MADE IN USA